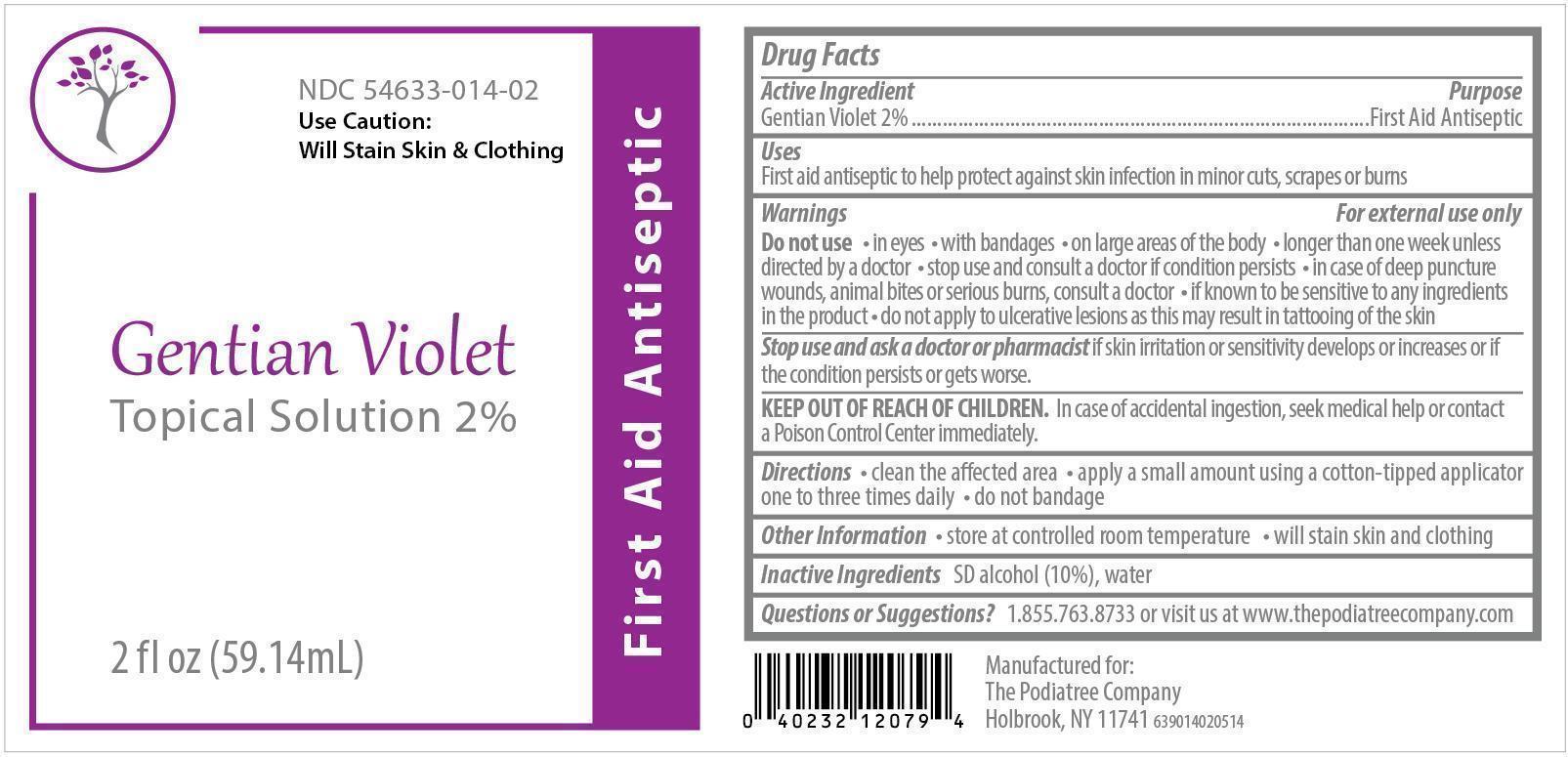 DRUG LABEL: Gentian Violet 2%
NDC: 54633-014 | Form: SOLUTION
Manufacturer: The Podiatree Company
Category: otc | Type: HUMAN OTC DRUG LABEL
Date: 20260108

ACTIVE INGREDIENTS: GENTIAN VIOLET 2 g/100 mL
INACTIVE INGREDIENTS: ALCOHOL; WATER

Active Ingredient

Gentian Violet 2%

Purpose

Antiseptic

Purpose

First aid antiseptic to help protect against skin infection in minor cuts, scrapes or burns

Warnings

For external use only

Do not use

in eyes; with bandages; on large areas of the body; longer than one week unless directed by a doctor; stop use and consult a doctor if condition persists; in case of deep puncture wounds, animal bites or serious burns, consult a doctor; if known to be sensitive to any ingredients in the product; do not apply to ulcerative lesions as this may result in tattooing of the skin.

Stop use and ask a doctor or pharmacist

if skin irritation or sensitivity develops or increases or if the condition persists or gets worse.

KEEP OUT OF REACH OF CHILDREN.

In case of accidental ingestion, seek medical help or contact a Poison Control Center immediately.

Directions

Clean the affected area. Apply a small amount using a cotton-tipped applicator one to three times daily. Do not bandage.

Other Information

Store at controlled room temperature. Will stain skin and clothing.

Inactive Ingredients

SD alcohol (10%), water

Questions or Suggestions?

1.855.763.8733 or visit us at www.thepodiatreecompany.com